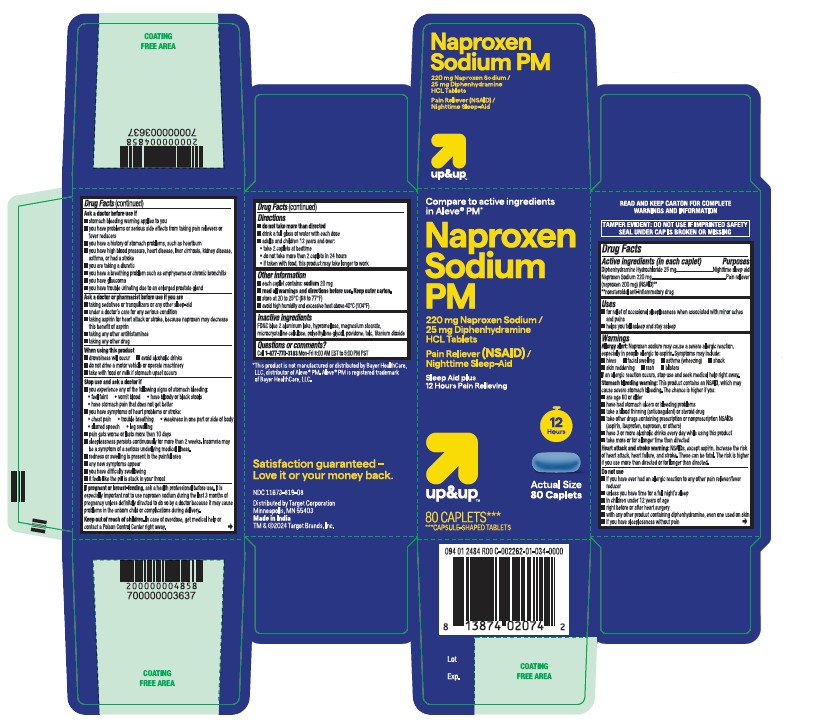 DRUG LABEL: Naproxen Sodium and Diphenhydramine HCL
NDC: 11673-819 | Form: TABLET
Manufacturer: TARGET CORPORATION
Category: otc | Type: HUMAN OTC DRUG LABEL
Date: 20251219

ACTIVE INGREDIENTS: DIPHENHYDRAMINE HYDROCHLORIDE 25 mg/1 1; NAPROXEN SODIUM 220 mg/1 1
INACTIVE INGREDIENTS: TALC; MAGNESIUM STEARATE; MICROCRYSTALLINE CELLULOSE; POVIDONE; POLYETHYLENE GLYCOL, UNSPECIFIED; TITANIUM DIOXIDE; HYPROMELLOSE 2910 (3 MPA.S); HYPROMELLOSE 2910 (6 MPA.S); FD&C BLUE NO. 2--ALUMINUM LAKE

Naproxen Sodium PM
220mg Naproxen Sodium/ 25mg Diphenhydramine HCL Tablets
Pain reliever (NSAID)/Nighttime sleep-aid
Sleep aid plus
12 hours pain relieving

Active ingredients (in each caplet)

Diphenhydramine
Hydrochloride 25 mg
Naproxen Sodium 220 mg
(naproxen 200 mg) (NSAID)*
* nonsteroidal anti-inflammatory drug

Purposes

Nighttime sleep aid

Pain reliever

Uses

• for relief of occasional sleeplessness when associated with minor aches and pains
• helps you fall asleep and stay asleep

Allergy alert:

Naproxen sodium may cause a severe allergic reaction, especially in people allergic to aspirin. Symptoms may include:
• hives • facial swelling • asthma (wheezing)
• shock • skin reddening • rash • blisters
If an allergic reaction occurs, stop use and seek medical help right away.

Stomach bleeding warning:

This product contains an NSAID, which may cause severe stomach bleeding. The chance is higher if you:
• are age 60 or older
• have had stomach ulcers or bleeding problems
• take a blood thinning (anticoagulant) or steroid drug
• take other drugs containing prescription or nonprescription NSAIDs (aspirin, ibuprofen, naproxen, or others)
• have 3 or more alcoholic drinks every day while using this product
• take more or for a longer time than directed

Heart attack and stroke warning:

NSAIDs, except aspirin, increase the risk of heart attack, heart failure, and stroke. These can be fatal. The risk is higher if use more than directed or for longer than directed.

Do not use

• if you have ever had an allergic reaction to any other pain reliever/fever reducer
• unless you have time for a full night’s sleep
• in children under 12 years of age
• right before or after heart surgery
• with any other product containing diphenhydramine, even one used on skin
• if you have sleeplessness without pain

Ask a doctor before use if

• stomach bleeding warning applies to you
• you have problems or serious side effects from taking pain relievers or fever reducers
• you have a history of stomach problems, such as heartburn
• you have high blood pressure, heart disease, liver cirrhosis, kidney disease, asthma, or had a stroke
• you are taking a diuretic
• you have a breathing problem such as emphysema or chronic bronchitis
• you have glaucoma
• you have trouble urinating due to an enlarged prostate gland

Ask a doctor or pharmacist before use if you are

• taking sedatives or tranquilizers, or any other sleep-aid
• under a doctor's care for any serious condition
• taking aspirin for heart attack or stroke, because naproxen may, decrease this benefit of aspirin
• taking any other antihistamines
• taking any other drug

When using this product

• drowsiness will occur
• avoid alcoholic drinks

• do not drive a motor vehicle or operate machinery
• take with food or milk if stomach upset occurs

Stop use and ask a doctor if

• you experience any of the following signs of stomach bleeding:
• feel faint

• vomit blood

• have bloody or black stools
• have stomach pain that does not get better
• you have symptoms heart problems or stroke:
• chest pain

• trouble breathing
• weakness in one part or side of body
• slurred speech

• leg swelling
• pain gets worse or lasts more than 10 days
• sleeplessness persists continuously for more than 2 weeks. Insomnia may be a symptom of a serious underlying medical illness.
• redness or swelling is present in the painful area
• any new symptoms appear
• you have difficulty swallowing
• it feels like the pill is stuck in your throat

If pregnant or breast-feeding,

ask a health professional before use. It is especially important not to use naproxen sodium during the last 3 months of pregnancy unless definitely directed to do so by a doctor because it may cause problems in the unborn child or complications during delivery.

Keep out of reach of children.

In case of overdose, get medical help or contact a Poison Control Center right away.

Directions

• do not take more than directed
• drink a full glass of water with each dose
• adults and children 12 years and over: take 2 caplets at bedtime
• do not take more than 2 caplets in 24 hours
• if taken with food, this product may take longer to work

Other information

• each caplet contains: sodium 20 mg
• read all warnings and directions before use. keep outer carton.
• store at 20 to 25°C (68 to 77°F)
• avoid high humidity and excessive heat above 40°C (104°F)

Inactive ingredients

FD&C blue 2 aluminum lake, hypromellose, magnesium stearate, microcrystalline cellulose, polyethylene glycol, povidone, talc, titanium dioxide.

Questions or comments?

Call 1-877-770-3183 Mon-Fri 8:00 AM EST to 5:00 PM PST.